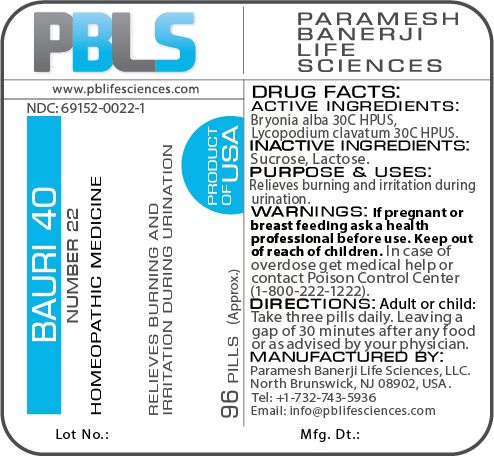 DRUG LABEL: Bauri 40 (Number 22)
NDC: 69152-0022 | Form: PELLET
Manufacturer: Paramesh Banerji Life Sciences LLC
Category: homeopathic | Type: HUMAN OTC DRUG LABEL
Date: 20180205

ACTIVE INGREDIENTS: LYCOPODIUM CLAVATUM SPORE 30 [hp_C]/1 1; BRYONIA ALBA ROOT 30 [hp_C]/1 1
INACTIVE INGREDIENTS: SUCROSE; LACTOSE

DRUG FACTS: Active Ingredients

Bryonia alba 30C HPUS, Lycopodium clavatum 30C HPUS

Inactive Ingredients

Sucrose, Lactose

Purpose

Relieves burning and irritation during urination

Uses

Relieves burning and irritation during urination

Warnings

If pregnant or breast feeding ask a health professional before use.

Keep out of reach of children. In case of overdose, get medical help or contact a Poison Control Center (1-800-222-1222) right away.

Direction

Adult or child: Take three pills daily. Leaving a gap of 30 minutes after any food or as advised by your physician.

Manufactured by

Paramesh Banerji Life Sciences, LLC.

North Brunswick, NJ 08902, USA.

Tel: +1-732-743-5936

Email: info@pblifesciences.com

Principal Display Panel

NDC: 69152-0022-1

Bauri 40

Number 22

Homeopathic Medicine

Relieves burning and irritation during urination

96 Pills (Approx.)

Product of USA